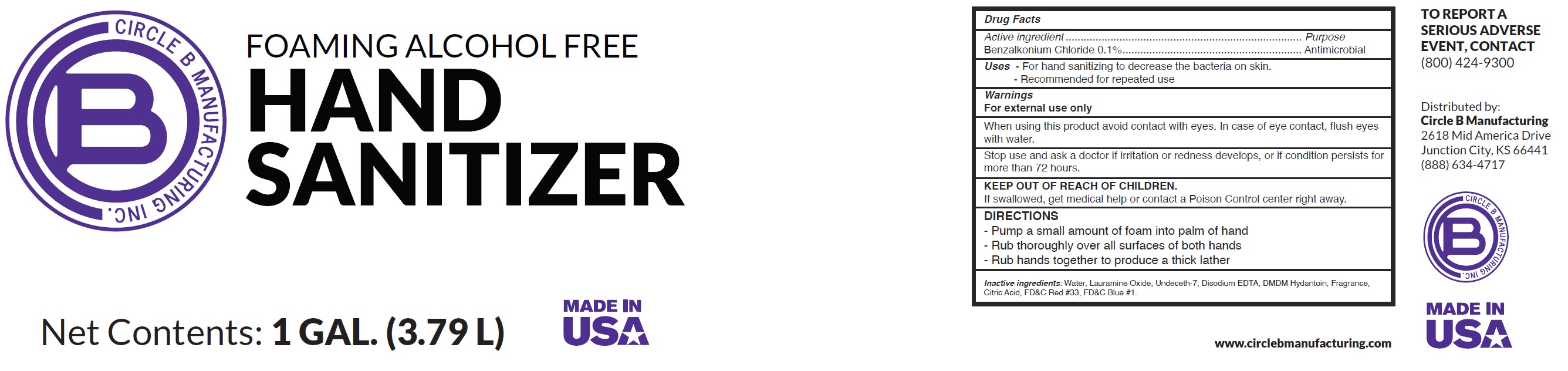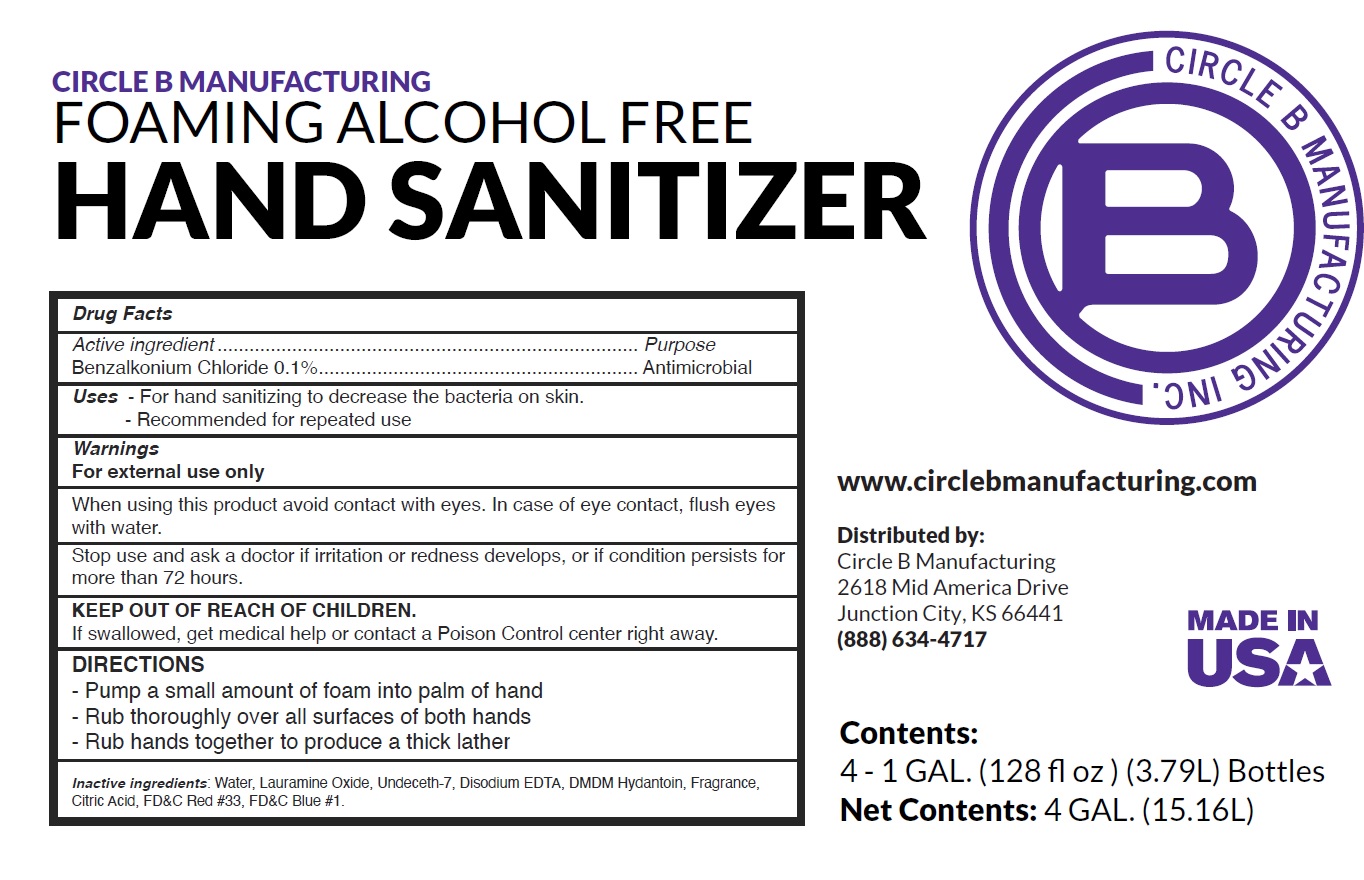 DRUG LABEL: Circle  B manufacturing foaming alcohol free Hand sanitizer
NDC: 81458-000 | Form: LIQUID
Manufacturer: Circle B Manufacturing, Inc.
Category: otc | Type: HUMAN OTC DRUG LABEL
Date: 20210201

ACTIVE INGREDIENTS: BENZALKONIUM CHLORIDE 1 mg/1 mL
INACTIVE INGREDIENTS: WATER; LAURAMINE OXIDE; UNDECETH-7; EDETATE DISODIUM ANHYDROUS; DMDM HYDANTOIN; CITRIC ACID MONOHYDRATE; FD&C BLUE NO. 1

Circle B manufacturing foaming alcohol free Hand sanitizer

Active ingredient

Benzalkonium Chloride 0.1%

Purpose

Antimicrobial

Uses

- For hand sanitizing to decrease the bacteria on skin.
- Recommended for repeated use

Warnings

For external use only

When using this product

avoid contact with eyes. In case of eye contact, flush eyes with water.

Stop use and ask a doctor

if irritation or redness develops, or if condition persists for more than 72 hours.

KEEP OUT OF REACH OF CHILDREN.

If swallowed, get medical help or contact a Poison Control center right away.

DIRECTIONS

- Pump a small amount of foam into palm of hand
- Rub thoroughly over all surfaces of both hands
- Rub hands together to produce a thick lather

Inactive ingredients:

Water, Lauramine Oxide, Undeceth-7, Disodium EDTA, DMDM Hydantoin, Fragrance, Citric Acid, FD&C Red #33, FD&C Blue #1.